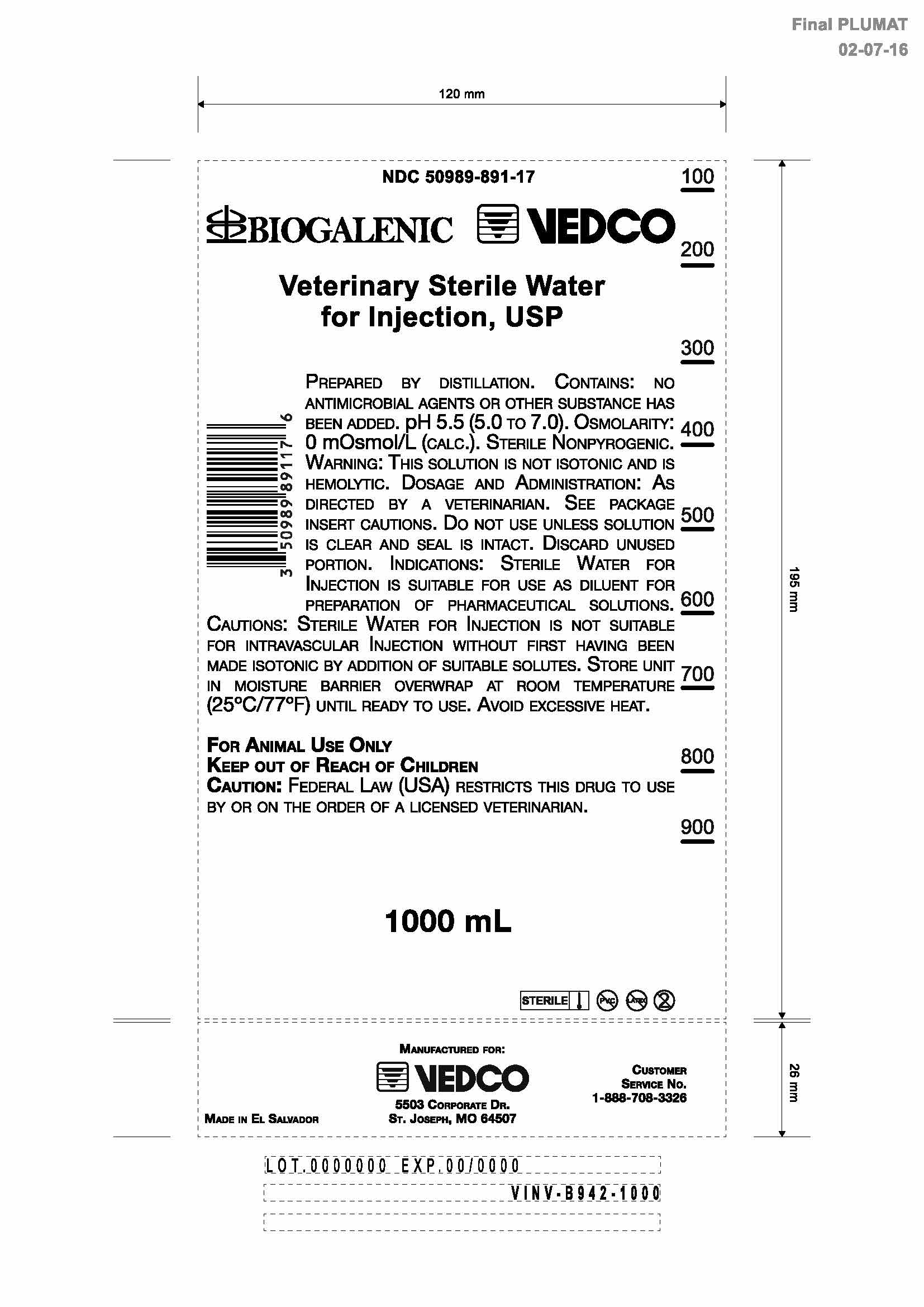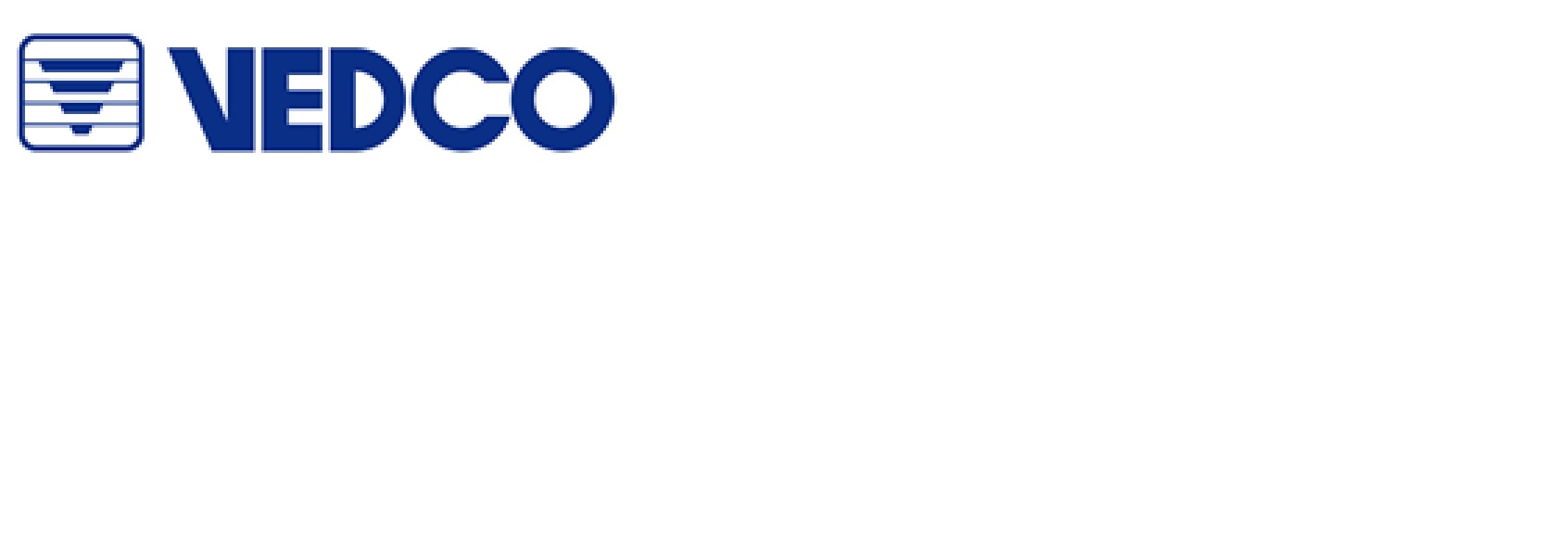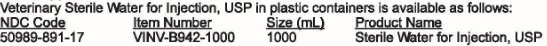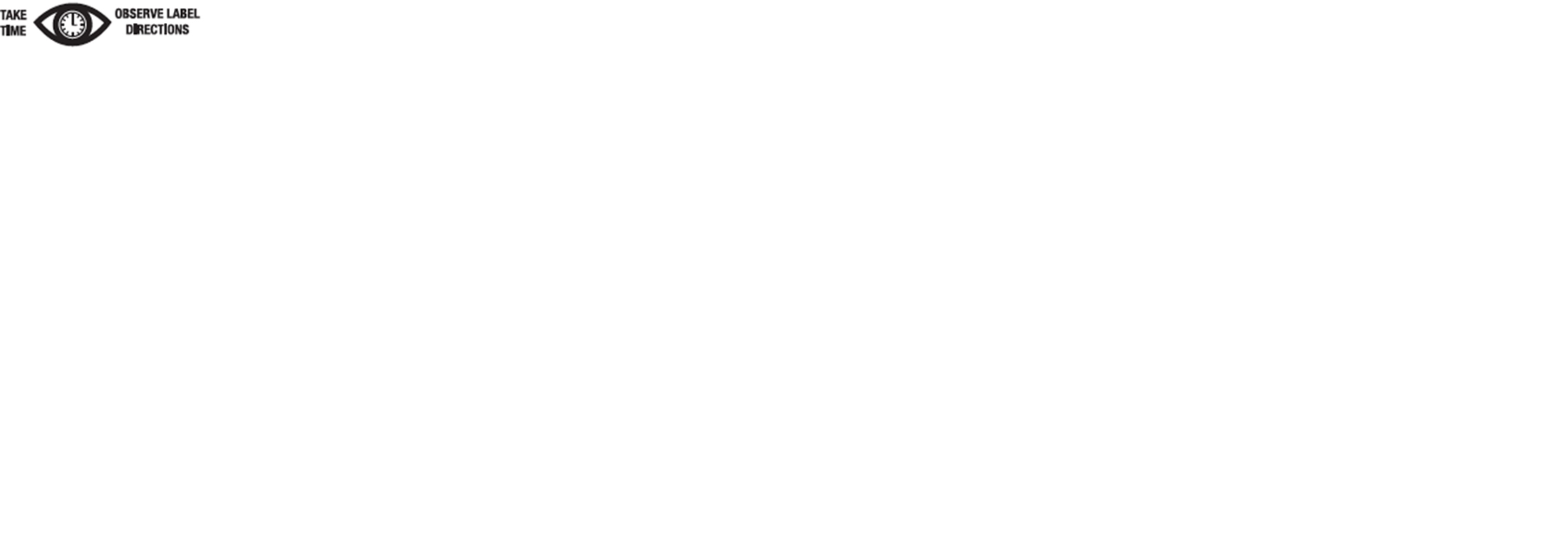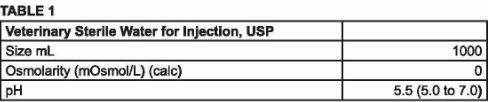 DRUG LABEL: Veterinary Sterile Water
                        
NDC: 50989-891 | Form: INJECTION
Manufacturer: Vedco, Inc.
Category: animal | Type: PRESCRIPTION ANIMAL DRUG LABEL
Date: 20160816

ACTIVE INGREDIENTS: WATER 100 g/100 mL

Veterinary Sterile Water For Injection, USP

For Animal Use Only

Indications

Veterinary Sterile Water for Injection is suitable for use as a diluent for the preparation of pharmaceutical solutions

Description

Prepared by distillation. Contains no antimicrobial agents or other substance has been added. Discard unused portion. Sterile, nonpyrogenic. Osmolarity and pH are shown in Table 1:

Contraindications:

None known

Warnings

This solution is not isotonic and is hemolytic.

Dosage and administration:

As directed by a veterinarian.

Cautions

Sterile water for Injection is not suitable for intravascular injection without first having been made isotonic by addition of suitable solutes. Do not use unless solution is clear and seal is intact. Discard unused portion.

How Supplied:

Veterinary Sterile Water for Injection, USP in plastic container is available as follows:

Plastic Container:
PVC Free, DEHP Free, Latex Free

Storage

Exposure of pharmaceutical products to heat should be minimized. Avoid excessive heat. It is recommended the product be stored in the moisture overwrap at room temperature (25^0C/77^0F), brief exposure up to (40^0C/104^0F)does not adversely affect the product.

Directions for use of plastic container

To Open

Tear overwrap down side at slit and remove solution container. Some opacity of the plastic due to moisture absorption during the sterilization process may be observed. This is normal and does not affect the solution quality or safety. The opacity will diminish gradually. Check for minute leaks by squeezing inner bag firmly. If leaks are found, discard solution as sterility may be impaired.

Not for injection, for irrigation only.

CAUTION: Federal law restricts this drug to use by or on the order of a licensed veterinarian

Manufacture for:

Vedco, Inc.

5503 Corporate Dr.

St. Joseph, MO 64507 USA

Printed in El Salvador

For a copy of the Safety Data Sheet (MSDS) or to report adverse reaction call Vedco, Inc.

Customer service at 1(888)708-3326

© 2015 Vedco, Inc.

Principal Display Panel

NDC 50989-891-17

BIOGALENIC VEDCO

Veterinary Sterile Water for Injection, USP